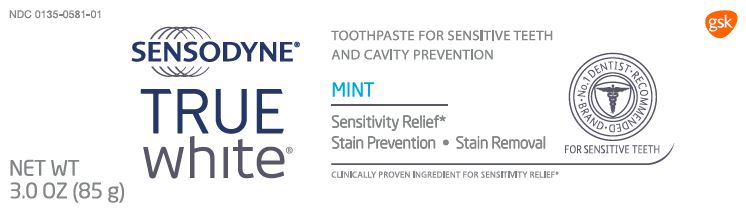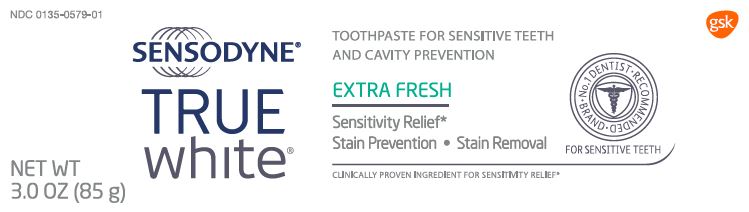 DRUG LABEL: Sensodyne

NDC: 0135-0581 | Form: PASTE
Manufacturer: Haleon US Holdings LLC
Category: otc | Type: HUMAN OTC DRUG LABEL
Date: 20240307

ACTIVE INGREDIENTS: POTASSIUM NITRATE 50 mg/1 g; SODIUM FLUORIDE 1.15 mg/1 g
INACTIVE INGREDIENTS: SORBITOL; WATER; GLYCERIN; HYDRATED SILICA; SODIUM TRIPOLYPHOSPHATE ANHYDROUS; POLYETHYLENE GLYCOL 400; TITANIUM DIOXIDE; SODIUM METHYL COCOYL TAURATE; COCAMIDOPROPYL BETAINE; XANTHAN GUM; SODIUM HYDROXIDE; SACCHARIN SODIUM

Drug Facts

Active ingredients

Potassium nitrate 5%**

Sodium fluoride 0.25% (0.16% w/v fluoride ion)

Purpose

Antihypersensitivity

Anticavity

Uses

- builds increasing protection against painful sensitivity of the teeth to cold, heat, acids, sweets, or contact.
- aids in the prevention of dental cavities.

Warnings

When using this product,

if irritation occurs discontinue use.

Stop use and ask a dentist if

- the problem persists or worsens. Sensitive teeth may indicate a serious problem that may need prompt care by a dentist.
- pain/sensitivity still persists after 4 weeks of use.

Keep out of reach of children.

If more than used for brushing is accidentally swallowed, get medical help or contact a Poison Control Center right away.

Directions

- Adults and children 12 years of age and older:
  - Apply at least a 1-inch strip of the product onto a soft bristle toothbrush.
  - Brush teeth thoroughly for at least 1 minute twice a day (morning and evening), and not more than 3 times a day, or as recommended by a dentist or doctor. Make sure to brush all sensitive areas of the teeth. Minimize swallowing. Spit out after brushing.
- Children under 12 years:Consult a dentist or doctor.

Other information

- store below 30°C (86°F)

Inactive ingredients

sorbitol, water, glycerin, hydrated silica, pentasodium triphosphate, PEG-8, flavor, titanium dioxide, sodium methyl cocoyl taurate, cocamidopropyl betaine, xanthan gum, sodium hydroxide, sodium saccharin

Questions or comments?

Call toll-free 1-866-844-2797

Principal Display Panel

NDC 0135-0581-01

SENSODYNE®

TRUE

white®

TOOTHPASTE FOR SENSITIVE TEETH AND CAVITY PREVENTION

MINT

Sensitivity Relief*

Stain Prevention • Stain Removal

CLINICALLY PROVEN INGREDIENT FOR SENSITIVITY RELIEF*

No. 1 DENTIST RECOMMENDED BRAND

FOR SENSITIVE TEETH

NET WT 3.0 OZ (85 g)

Brushing with abrasive toothpaste can wear the sensitive areas of your teeth. Sensodyne ®True White ®has the lowest abrasion formulation ever in a Sensodyne ®toothpaste.

With twice daily brushing it:

- is proven to relieve sensitivity pain
- helps to gently whiten your teeth
- leaves a protective shield to help prevent new stains forming
- freshens breath, fights cavities and helps keep gums healthy

*with twice daily brushing

**maximum FDA sensitivity active ingredient

GSKConsumer Healthcare

Warren, NJ 07059

Trademarks are owned by or licensed to the GSK group of companies.

©2015 GSK group of companies or its licensor. All rights reserved

ALWAYS FOLLOW THE LABEL

105639XA

Principal Display Panel

NDC 0135-0579-01

SENSODYNE®

TRUE

white®

TOOTHPASTE FOR SENSITIVE TEETH AND CAVITY PREVENTION

EXTRA FRESH

Sensitivity Relief*

Stain Prevention • Stain Removal

CLINICALLY PROVEN INGREDIENT FOR SENSITIVITY RELIEF*

No. 1 DENTIST RECOMMENDED BRAND

FOR SENSITIVE TEETH

NET WT 3.0 OZ (85 g)

Brushing with abrasive toothpaste can wear the sensitive areas of your teeth. Sensodyne ®True White ®has the lowest abrasion formulation ever in a Sensodyne ®toothpaste.

With twice daily brushing it:

- is proven to relieve sensitivity pain
- helps to gently whiten your teeth
- leaves a protective shield to help prevent new stains forming
- freshens breath, fights cavities and helps keep gums healthy

*with twice daily brushing

**maximum FDA sensitivity active ingredient

GSKConsumer Healthcare

Warren, NJ 07059

Trademarks are owned by or licensed to the GSK group of companies.

©2015 GSK group of companies or its licensor. All rights reserved.

ALWAYS FOLLOW THE LABEL

105640XA